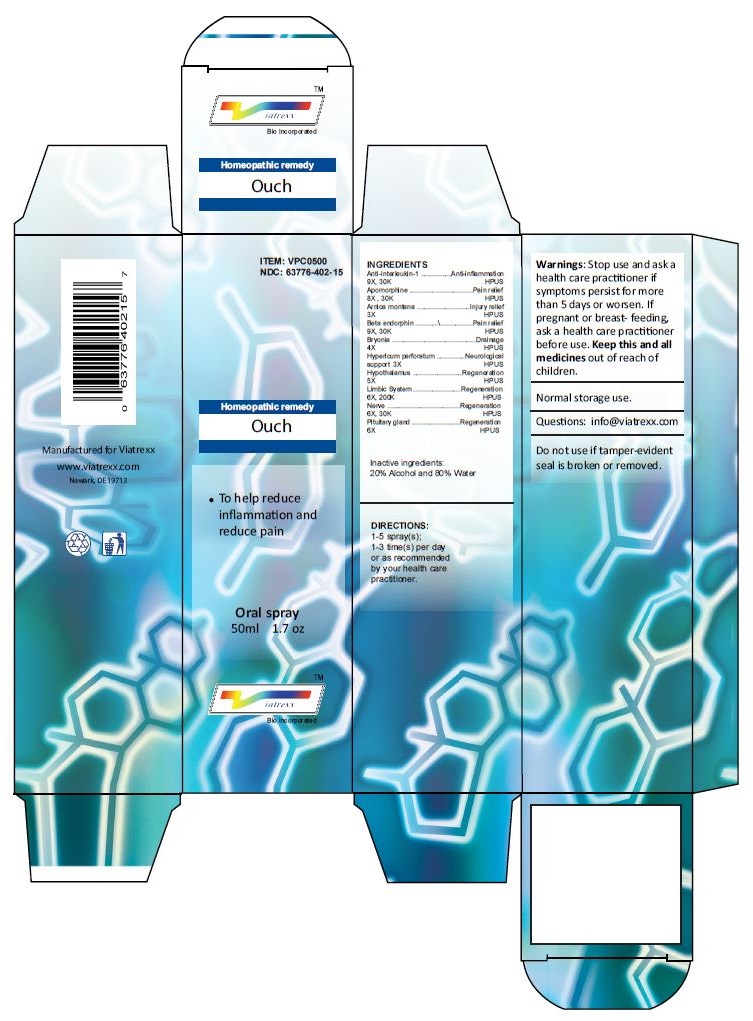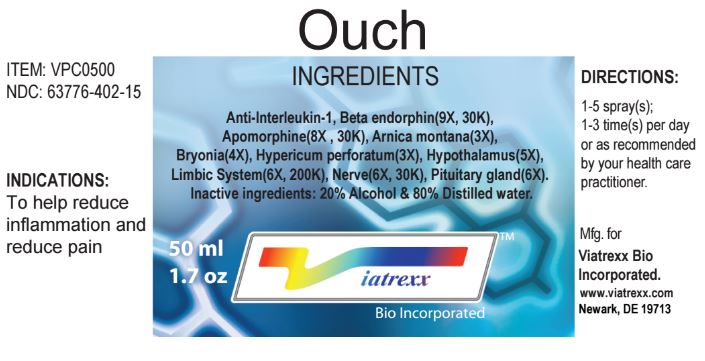 DRUG LABEL: Ouch
NDC: 63776-402 | Form: SPRAY
Manufacturer: VIATREXX BIO INCORPORATED
Category: homeopathic | Type: HUMAN OTC DRUG LABEL
Date: 20221130

ACTIVE INGREDIENTS: ANTI-INTERLEUKIN-1.ALPHA. IMMUNOGLOBULIN G RABBIT 30 [kp_C]/1 mL; APOMORPHINE 30 [kp_C]/1 mL; ARNICA MONTANA 3 [hp_X]/1 mL; METENKEFALIN 30 [kp_C]/1 mL; BRYONIA ALBA ROOT 4 [hp_X]/1 mL; HYPERICUM PERFORATUM 3 [hp_X]/1 mL; BOS TAURUS HYPOTHALAMUS 5 [hp_X]/1 mL; SUS SCROFA HYPOTHALAMUS 5 [hp_X]/1 mL; BOS TAURUS LIMBIC SYSTEM 200 [kp_C]/1 mL; SUS SCROFA LIMBIC SYSTEM 200 [kp_C]/1 mL; BOS TAURUS NERVE 30 [kp_C]/1 mL; SUS SCROFA NERVE 30 [kp_C]/1 mL; BOS TAURUS PITUITARY GLAND 6 [hp_X]/1 mL; SUS SCROFA PITUITARY GLAND 6 [hp_X]/1 mL
INACTIVE INGREDIENTS: WATER; ALCOHOL

Ouch

Active Ingredients

Anti-Interleukin-1 9X 30K, Apomorphine 8X 30K, Arnica montana 3X, Beta endorphin 9X 30K, Bryonia 4X, Hypericum perforatum 3X, Hypothalamus 5X, Limbic System 6X 200K, Nerve 6X 30K, Pituitary gland 6X

Purpose

Anti-Interleukin-1 | Anti-inflammation
Apomorphine | Pain relief
Arnica montana | Injury relief
Beta endorphin | Pain relief
Bryonia | Drainage
Hypericum perforatum | Neurological support
Hypothalamus | Regeneration
Limbic System | Regeneration
Nerve | Regeneration
Pituitary gland | Regeneration

Uses

To help reduce inflammation and reduce pain

Warnings

Stop use and ask a health care practitioner if symptoms persist for more than 5 days or worsen. If pregnant or breastfeeding, ask a health care practitioner before use.

KEEP OUT OF REACH OF CHILDREN

Keep this and all medicines out of reach of children.

Directions

1-5 spray(s); 1-3 time(s) per day or as recommended by your health care practitioner.

Other Ingredients

Alcohol and Water

Other Information

Normal storage use.
Do not use if tamper-evident seal is broken or removed.

Questions

info@viatrexx.com

Principal Display Panel

ITEM: VPC0500
NDC 63776-402-15
Homeopathic remedy
Ouch
• To help reduce inflammation and reduce pain
Oral spray
50ml 1.7 oz
Viatrexx™ Bio Incorporated
Manufactured by Viatrexx
www.viatrexx.com
Newark, DE 19713

Ouch
50 mL
1.7 oz
Viatrexx™ Bio Incorporated
ITEM: VPC0500
NDC: 63776-402-15
INDICATIONS:
To help reduce inflammation and reduce pain
DIRECTIONS:
1-5 spray(s); 1-3 time(s) per day or as recommended by your health care practitioner.
Mfg. for
Viatrexx Bio Incorporated.
www.viatrexx.com
Newark, DE 19713